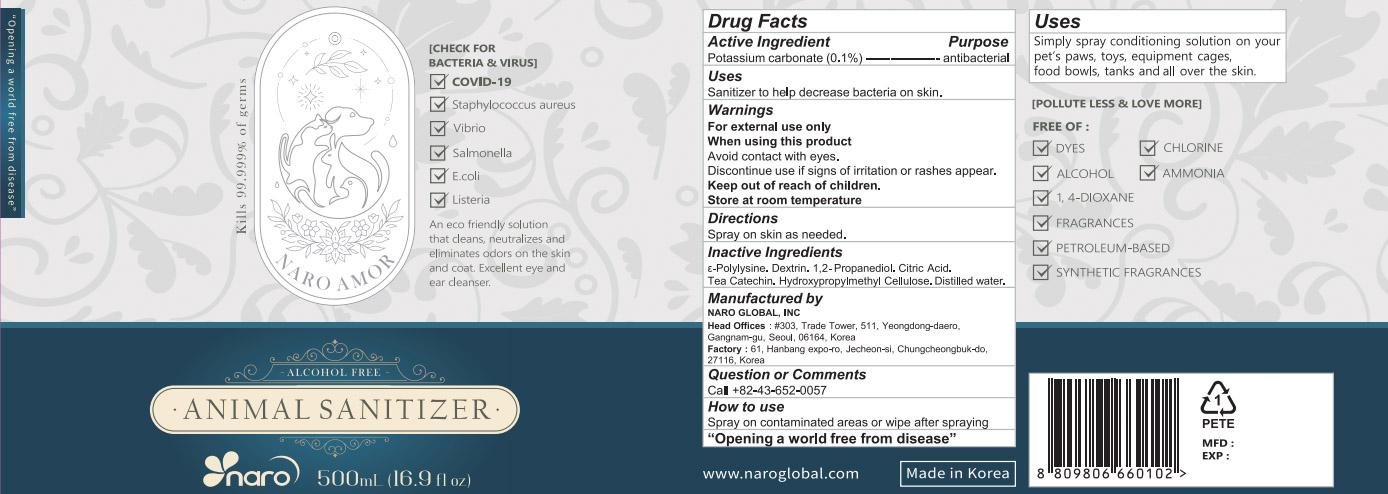 DRUG LABEL: NARO AMOR
NDC: 81936-0004 | Form: LIQUID
Manufacturer: NARO Global Inc.
Category: animal | Type: OTC ANIMAL DRUG LABEL
Date: 20211005

ACTIVE INGREDIENTS: POTASSIUM CARBONATE 0.1 g/100 mL
INACTIVE INGREDIENTS: WATER; CALCIUM HYDROXIDE

ACTIVE INGREDIENT

Potassium carbonate

INACTIVE INGREDIENT

ε-Polylysine.Dextrin.1,2-Propanediol.Citric Acid.Tea Catechin. Hydroxypropylmethyl Cellulose.Distilled water.

PURPOSE

Sanitizer to help decrease bacteria on skin

Keep out of reach of children

INDICATIONS AND USAGE

Spray on the skin (animal) as needed

WARNINGS

Use only according to instructuins.

Keep out of reach of children.

Avoid contact with eyes.

In case of eye contact, flush thoroughly with water.

DOSAGE AND ADMINISTRATION

For external use only